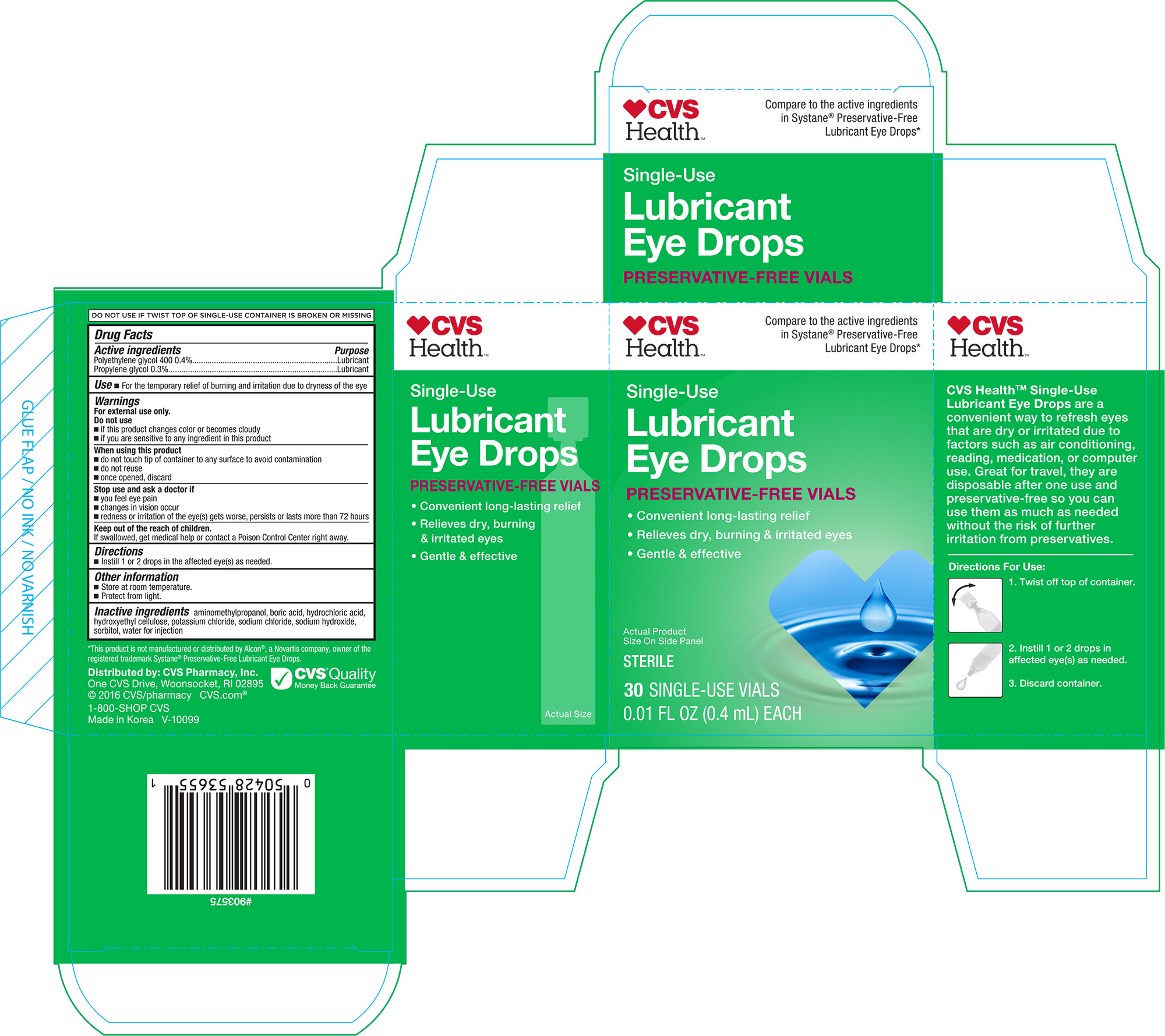 DRUG LABEL: Cvs Single Use Lubricant Eye Drops
NDC: 10564-6553 | Form: SOLUTION/ DROPS
Manufacturer: Bershtel Enterprises LLC
Category: otc | Type: HUMAN OTC DRUG LABEL
Date: 20180301

ACTIVE INGREDIENTS: PROPYLENE GLYCOL 3 mg/1 1; POLYETHYLENE GLYCOL 400 4 mg/1 1
INACTIVE INGREDIENTS: AMINOMETHYLPROPANOL; BORIC ACID; HYDROCHLORIC ACID; SORBITOL; WATER; POTASSIUM CHLORIDE; SODIUM CHLORIDE; SODIUM HYDROXIDE

ACTIVE INGREDIENT

Active ingredients PurposePolyethylene glycol 400 0.4%......................................LubricantPropylene glycrol 0.3%...............................................Lubricant

PURPOSE

UseFor the temporary relief of burning and irritation due to dryness of the eye

Warnings For external use only.

WHEN USING

When using this productdo not touch tip of container to any surface to avoid contaminationdo not reuseonce opened, discard

Stop use and ask a doctor ifyou feel eye painchanges in vision occurredness or irritation of the eye(s) get worse, persists or lasts more than 72 hours

Keep out of reach of children.If swallowed, get medical help or contact a Poison Control Center right away.

Ophthalmic - Administration to the external eye.

INDICATIONS AND USAGE

Directions Instill 1 or 2 drops in the affected eye(s) as needed.

Other information Store at room temperature. Protect from light.

INACTIVE INGREDIENT

Inactive ingredientsaminomethylpropanol, boric acid, hydrochloric acid, hydroxyethyl cellulose, potassium chloride, sodium chloride, sodium hydroxide, sorbitol, water for injection